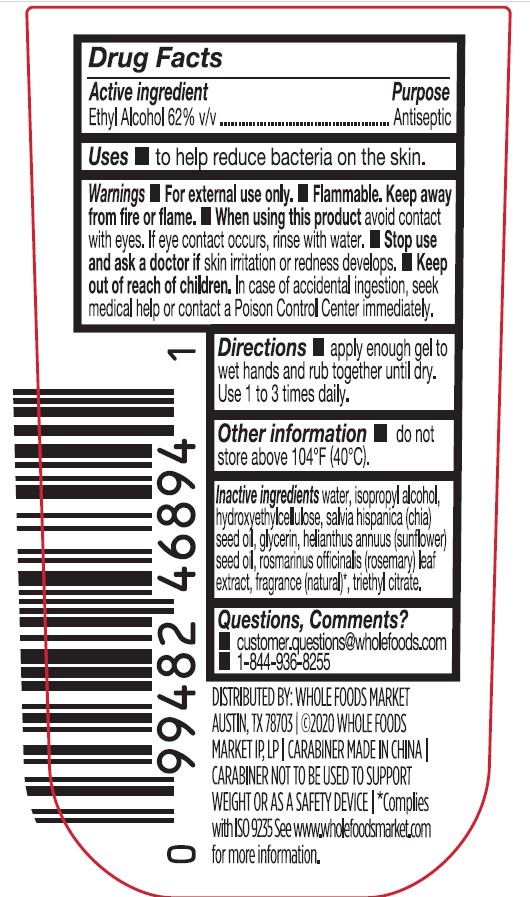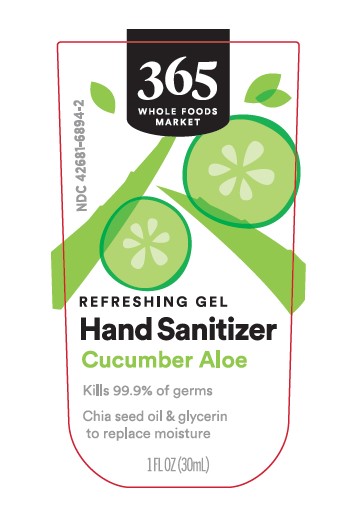 DRUG LABEL: Hand Sanitizer
NDC: 42681-6894 | Form: GEL
Manufacturer: Whole Foods Market, Inc.
Category: otc | Type: HUMAN OTC DRUG LABEL
Date: 20241102

ACTIVE INGREDIENTS: ALCOHOL 62 mL/100 mL
INACTIVE INGREDIENTS: WATER; ISOPROPYL ALCOHOL; HYDROXYETHYL CELLULOSE (100 MPA.S AT 2%); CHIA SEED OIL; GLYCERIN; SUNFLOWER OIL; ROSEMARY; TRIETHYL CITRATE

Whole Foods Cucumber Aloe Hand Sanitizer Gel 1 fl oz

Active Ingredient

Ethyl Alcohol 62% v/v

Purpose

Antiseptic

WARNINGS

For external use only. Flammable. Keep away from fire or flame.

WHEN USING

When using this productavoid contact with eyes. If eye contact occurs, rinse with water.

Stop use and ask a doctor ifskin irritation or redness develops.

Keep out of reach of children.In case of accidental ingestion, seek medical help or contact a Poison Control Center immediately.

DOSAGE AND ADMINISTRATION

Directionsapply enough gel to wet hands and rub together until dry. Use 1 to 3 times daily.

STORAGE AND HANDLING

Other informationdo not store above 104°F (40°C).

Questions, Comments?

customer.questions@wholefoods.com

1-844-963-8255

INACTIVE INGREDIENT

Inactive ingredientswater, isopropyl alcohol, hydroxyethylcellulose, salvia hispanica (chia) seed oil, glycerin, helianthus annuus (sunflower) seed oil, rosmarinus officinalis (rosemary) leaf extract, fragrance (natural), triethyl citrate.

*Complies with ISO 9235. See www.wholefoodsmarket.com for more information.